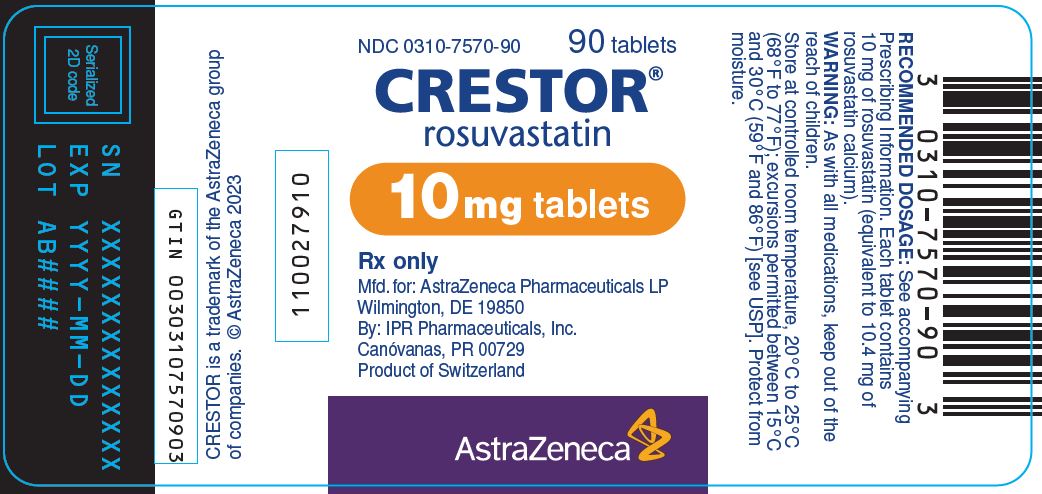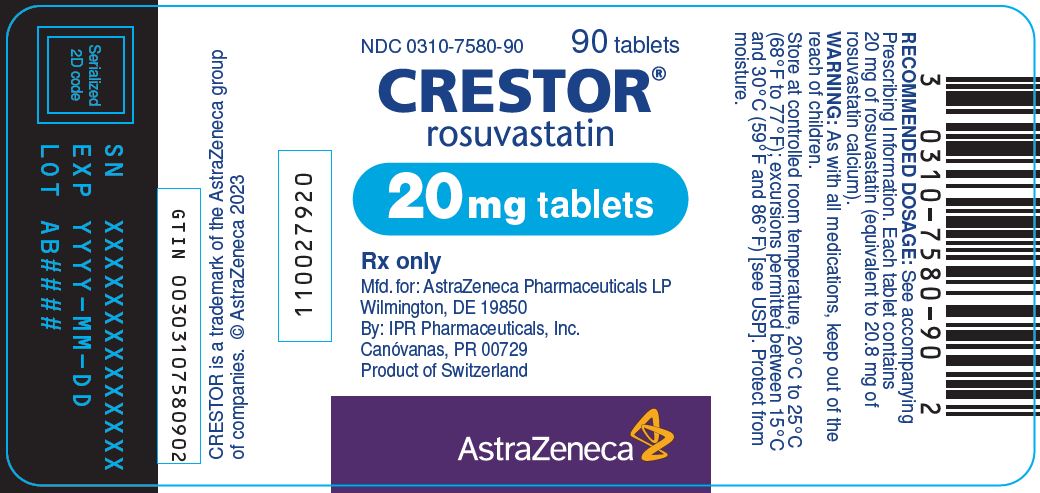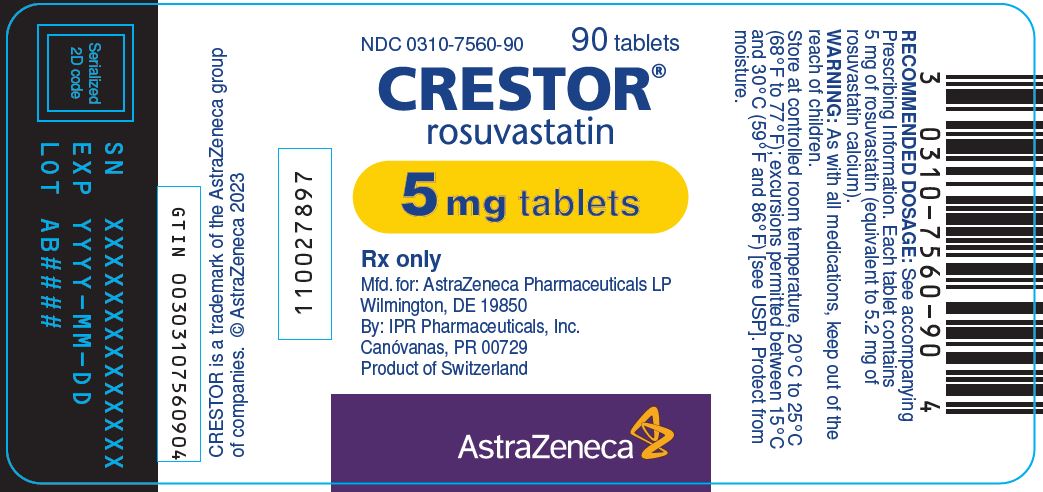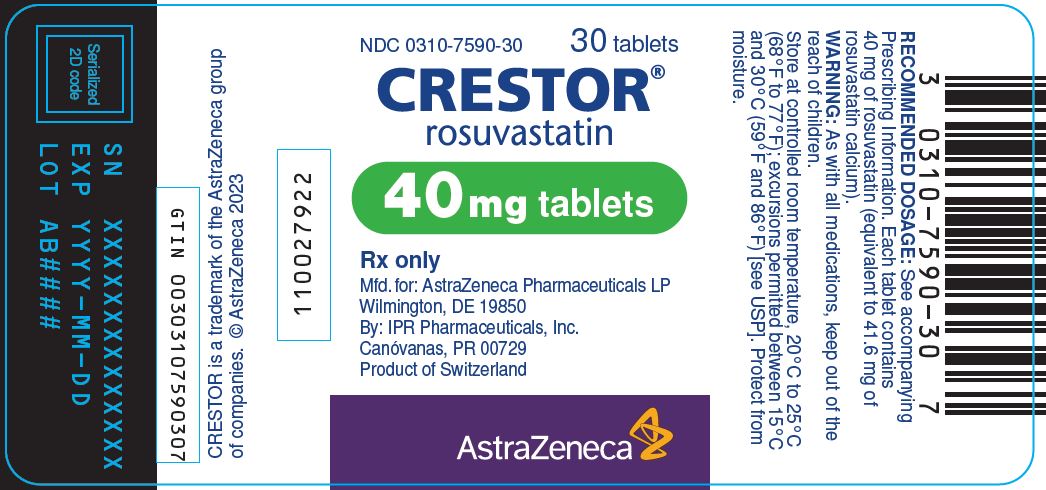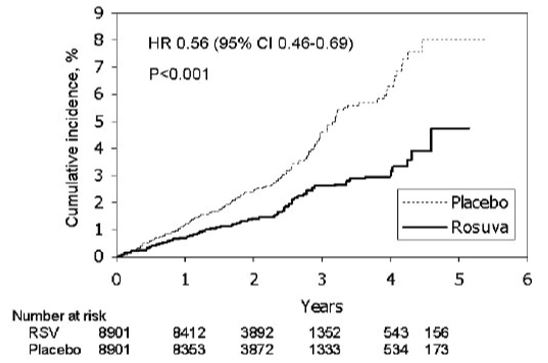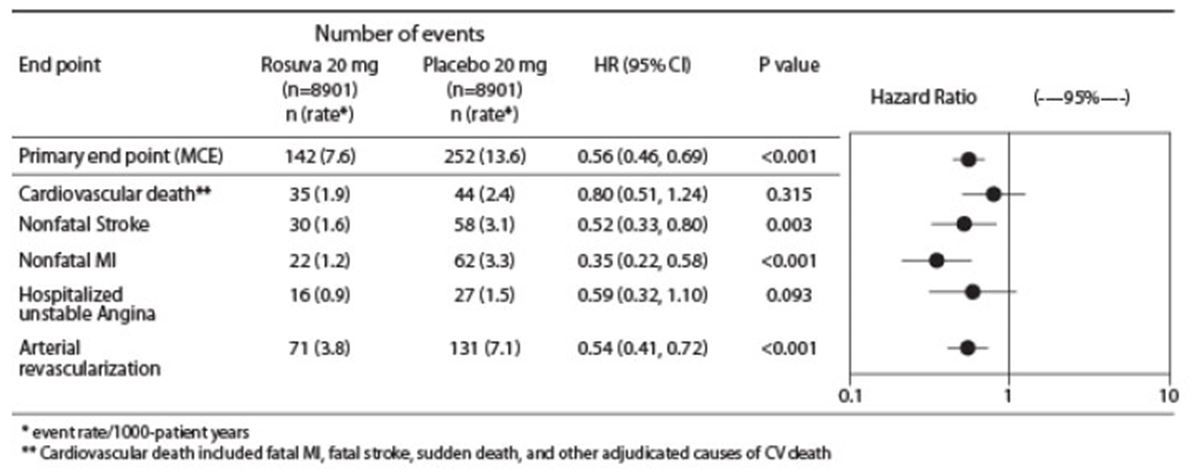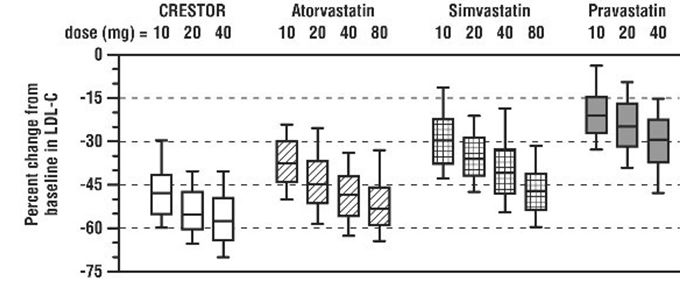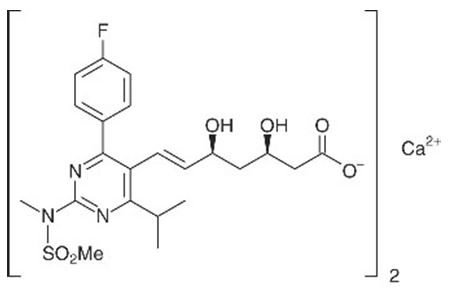 DRUG LABEL: Crestor
NDC: 0310-7560 | Form: TABLET, FILM COATED
Manufacturer: AstraZeneca Pharmaceuticals LP
Category: prescription | Type: HUMAN PRESCRIPTION DRUG LABEL
Date: 20251218

ACTIVE INGREDIENTS: ROSUVASTATIN CALCIUM 5 mg/1 1
INACTIVE INGREDIENTS: FERRIC OXIDE YELLOW; HYPROMELLOSE, UNSPECIFIED; LACTOSE MONOHYDRATE; MICROCRYSTALLINE CELLULOSE; TITANIUM DIOXIDE; TRIACETIN

HIGHLIGHTS OF PRESCRIBING INFORMATION

These highlights do not include all the information needed to use CRESTOR safely and effectively. See full prescribing information for CRESTOR.
CRESTOR (rosuvastatin) tablets, for oral use
Initial U.S. Approval: 2003

RECENT MAJOR CHANGES

Indications and Usage (1) 07/2024

1 INDICATIONS AND USAGE

CRESTOR is an HMG Co‑A reductase inhibitor (statin) indicated: (1)

- To reduce the risk of major adverse cardiovascular (CV) events (CV death, nonfatal myocardial infarction, nonfatal stroke, or an arterial revascularization procedure) in adults without established coronary heart disease who are at increased risk of CV disease based on age, high-sensitivity C-reactive protein (hsCRP) ≥2 mg/L, and at least one additional CV risk factor.
- As an adjunct to diet to:
  ∘ reduce LDL-C in adults with primary hyperlipidemia.
  ∘ reduce LDL-C and slow the progression of atherosclerosis in adults.
  ∘ reduce LDL-C in adults and pediatric patients aged 8 years and older with heterozygous familial hypercholesterolemia (HeFH).
- As an adjunct to other LDL-C-lowering therapies, or alone if such treatments are unavailable, to reduce LDL-C in adults and pediatric patients aged 7 years and older with homozygous familial hypercholesterolemia (HoFH).
- As an adjunct to diet for the treatment of adults with:
  ∘ Primary dysbetalipoproteinemia.
  ∘ Hypertriglyceridemia.

2 DOSAGE AND ADMINISTRATION

Take orally with or without food, at any time of day. (2.1)

Assess LDL-C when clinically appropriate, as early as 4 weeks after initiating CRESTOR, and adjust dosage if necessary. (2.1)

Adults: Recommended dosage range is 5 to 40 mg once daily. (2.1)

Pediatric Patients with HeFH: Recommended dosage range is 5 to 10 mg once daily for patients aged 8 to less than 10 years of age, and 5 to 20 mg once daily for patients aged 10 years and older. (2.2)

Pediatric Patients with HoFH: Recommended dosage is 20 mg once daily for patients aged 7 years and older. (2.2)

Asian Patients: Initiate at 5 mg once daily. Consider risks and benefits of treatment if not adequately controlled at doses up to 20 mg once daily. (2.4)

Patients with Severe Renal Impairment (not on hemodialysis): Initiate at 5 mg once daily; do not exceed 10 mg once daily. (2.5)

See full prescribing information for CRESTOR dosage and administration modifications due to drug interactions. (2.6)

3 DOSAGE FORMS AND STRENGTHS

Tablets: 5 mg, 10 mg, 20 mg, and 40 mg of rosuvastatin. (3)

4 CONTRAINDICATIONS

Acute liver failure or decompensated cirrhosis. (4)

Hypersensitivity to rosuvastatin or any excipients in CRESTOR. (4)

5 WARNINGS AND PRECAUTIONS

- Myopathy and Rhabdomyolysis: Risk factors include age 65 years or greater, uncontrolled hypothyroidism, renal impairment, concomitant use with certain other drugs, and higher CRESTOR dosage. Asian patients may be at higher risk for myopathy. Discontinue CRESTOR if markedly elevated CK levels occur or myopathy is diagnosed or suspected. Temporarily discontinue CRESTOR in patients experiencing an acute or serious condition at high risk of developing renal failure secondary to rhabdomyolysis. Inform patients of the risk of myopathy and rhabdomyolysis when starting or increasing CRESTOR dosage. Instruct patients to promptly report unexplained muscle pain, tenderness, or weakness, particularly if accompanied by malaise or fever. (5.1)
- Immune-Mediated Necrotizing Myopathy (IMNM): Rare reports of IMNM, an autoimmune myopathy, have been reported with statin use. Discontinue CRESTOR if IMNM is suspected. (5.2)
- Hepatic Dysfunction: Increases in serum transaminases have occurred, some persistent. Rare reports of fatal and non-fatal hepatic failure have occurred. Consider testing liver enzymes before initiating therapy and as clinically indicated thereafter. If serious hepatic injury with clinical symptoms and/or hyperbilirubinemia or jaundice occurs, promptly discontinue CRESTOR. (5.3)

6 ADVERSE REACTIONS

Most frequent adverse reactions (rate ≥2%) are headache, nausea, myalgia, asthenia, and constipation. (6.1)

To report SUSPECTED ADVERSE REACTIONS, contact AstraZeneca at 1-800-236-9933 or FDA at 1-800-FDA-1088 or www.fda.gov/medwatch.

7 DRUG INTERACTIONS

See full prescribing information for details regarding concomitant use of CRESTOR with other drugs that increase the risk of myopathy and rhabdomyolysis. (7.1)

Aluminum and Magnesium Hydroxide Combination Antacids: Administer CRESTOR at least 2 hours before the antacid. (7.2)

Wafarin: Obtain INR prior to starting CRESTOR. Monitor INR frequently until stable upon initiation, dose titration or discontinuation. (7.3)

8 USE IN SPECIFIC POPULATIONS

- Pregnancy: May cause fetal harm. (8.1)
- Lactation: Breastfeeding not recommended during treatment with CRESTOR. (8.2)

FULL PRESCRIBING INFORMATION

1 INDICATIONS AND USAGE

CRESTOR is indicated:

- To reduce the risk of major adverse cardiovascular (CV) events (CV death, nonfatal myocardial infarction, nonfatal stroke, or an arterial revascularization procedure) in adults without established coronary heart disease who are at increased risk of CV disease based on age, high-sensitivity C-reactive protein (hsCRP) ≥2 mg/L, and at least one additional CV risk factor.
- As an adjunct to diet to:
  ∘ Reduce low-density lipoprotein cholesterol (LDL-C) in adults with primary hyperlipidemia.
  ∘ Reduce LDL-C and slow the progression of atherosclerosis in adults.
  ∘ Reduce LDL-C in adults and pediatric patients aged 8 years and older with heterozygous familial hypercholesterolemia (HeFH).
- As an adjunct to other LDL-C-lowering therapies, or alone if such treatments are unavailable, to reduce LDL-C in adults and pediatric patients aged 7 years and older with homozygous familial hypercholesterolemia (HoFH).
- As an adjunct to diet for the treatment of adults with:
  ∘ Primary dysbetalipoproteinemia.
  ∘ Hypertriglyceridemia.

2 DOSAGE AND ADMINISTRATION

2.1 General Dosage and Administration Information

- Administer CRESTOR orally as a single dose at any time of day, with or without food. Swallow the tablets whole.
- Assess LDL-C when clinically appropriate, as early as 4 weeks after initiating CRESTOR, and adjust the dosage if necessary.
- If a dose is missed, advise patients not to take an extra dose. Resume treatment with the next dose.
- When taking CRESTOR with an aluminum and magnesium hydroxide combination antacid, administer CRESTOR at least 2 hours before the antacid [see Drug Interactions (7.2)].

2.2 Recommended Dosage in Adult Patients

- The dosage range for CRESTOR is 5 to 40 mg orally once daily.
- The recommended dose of CRESTOR depends on a patient’s indication for usage, LDL-C, and individual risk for CV events.

2.3 Recommended Dosage in Pediatric Patients

Dosage in Pediatric Patients 8 Years of Age and Older with HeFH

The recommended dosage range is 5 mg to 10 mg orally once daily in patients aged 8 years to less than 10 years and 5 mg to 20 mg orally once daily in patients aged 10-years and older.

Dosage in Pediatric Patients 7 Years of Age and Older with HoFH

The recommended dosage is 20 mg orally once daily.

2.4 Dosing in Asian Patients

Initiate CRESTOR at 5 mg once daily due to increased rosuvastatin plasma concentrations. Consider the risks and benefits of CRESTOR when treating Asian patients not adequately controlled at doses up to 20 mg once daily [see Warnings and Precautions (5.1), Use in Specific Populations (8.8), and Clinical Pharmacology (12.3)].

2.5 Recommended Dosage in Patients with Renal Impairment

In patients with severe renal impairment (CLcr less than 30 mL/min/1.73 m2) not on hemodialysis, the recommended starting dosage is 5 mg once daily and should not exceed 10 mg once daily [see Warnings and Precautions (5.1) and Use in Specific Populations (8.6)].

There are no dosage adjustment recommendations for patients with mild and moderate renal impairment.

2.6 Dosage Modifications Due to Drug Interactions

Table 1 displays dosage modifications for CRESTOR due to drug interactions [see Warnings and Precautions (5.1) and Drug Interactions (7.1)].

Table 1: CRESTOR Dosage Modifications Due to Drug Interactions
Concomitantly Used Drug | CRESTOR Dosage Modifications
Cyclosporine | Do not exceed 5 mg once daily.
Teriflunomide | Do not exceed 10 mg once daily.
Enasidenib | Do not exceed 10 mg once daily.
Capmatinib | Do not exceed 10 mg once daily.
Fostamatinib | Do not exceed 20 mg once daily.
Febuxostat | Do not exceed 20 mg once daily.
Gemfibrozil | Avoid concomitant use. If used concomitantly, initiate at 5 mg once daily and do not exceed 10 mg once daily.
Tafamidis | Avoid concomitant use. If used concomitantly, initiate at 5 mg once daily and do not exceed 20 mg once daily.
Antiviral Medications
- Sofbuvir/velpatasvir/voxilaprevir - Ledipasvir/sofosbuvir | Concomitant use not recommended.
- Simeprevir - Dasabuvir/ombitasvir/paritaprevir/ritonavir - Elbasvir/Grazoprevir - Sofosbuvir/Velpatasvir - Glecaprevir/Pibrentasvir - Atazanavir/Ritonavir - Lopinavir/Ritonavir | Initiate at 5 mg once daily. Do not exceed 10 mg once daily.
Darolutamide | Do not exceed 5 mg once daily.
Regorafenib | Do not exceed 10 mg once daily.

3 DOSAGE FORMS AND STRENGTHS

CRESTOR tablets:

- 5 mg of rosuvastatin: yellow, round, biconvex, coated tablets. Debossed “ZD4522” and “5” on one side of the tablet.
- 10 mg of rosuvastatin: pink, round, biconvex, coated tablets. Debossed “ZD4522” and “10” on one side of the tablet.
- 20 mg of rosuvastatin: pink, round, biconvex, coated tablets. Debossed “ZD4522” and “20” on one side of the tablet.
- 40 mg of rosuvastatin: pink, oval, biconvex, coated tablets. Debossed “ZD4522” on one side and “40” on the other side of the tablet.

4 CONTRAINDICATIONS

CRESTOR is contraindicated in the following conditions:

- Acute liver failure or decompensated cirrhosis [see Warnings and Precautions (5.3)].
- Hypersensitivity to rosuvastatin or any excipients in CRESTOR. Hypersensitivity reactions including rash, pruritus, urticaria, and angioedema have been reported with CRESTOR [see Adverse Reactions (6.1)].

5 WARNINGS AND PRECAUTIONS

5.1 Myopathy and Rhabdomyolysis

CRESTOR may cause myopathy [muscle pain, tenderness, or weakness associated with elevated creatine kinase (CK)] and rhabdomyolysis. Acute kidney injury secondary to myoglobinuria and rare fatalities have occurred as a result of rhabdomyolysis with statins, including CRESTOR.

Risk Factors for Myopathy

Risk factors for myopathy include age 65 years or greater, uncontrolled hypothyroidism, renal impairment, concomitant use with certain other drugs (including other lipid-lowering therapies), and higher CRESTOR dosage. Asian patients on CRESTOR may be at higher risk for myopathy [see Drug Interactions (7.1) and Use in Specific Populations (8.8)]. The myopathy risk is greater in patients taking CRESTOR 40 mg daily compared with lower CRESTOR dosages.

Steps to Prevent or Reduce the Risk of Myopathy and Rhabdomyolysis

The concomitant use of CRESTOR with cyclosporine or gemfibrozil is not recommended. CRESTOR dosage modifications are recommended for patients taking certain antiviral medications, darolutamide, and regorafenib [see Dosage and Administration (2.6)]. Niacin, fibrates, and colchicine may also increase the risk of myopathy and rhabdomyolysis [see Drug Interactions (7.1)].

Discontinue CRESTOR if markedly elevated CK levels occur or if myopathy is either diagnosed or suspected. Muscle symptoms and CK elevations may resolve if CRESTOR is discontinued. Temporarily discontinue CRESTOR in patients experiencing an acute or serious condition at high risk of developing renal failure secondary to rhabdomyolysis (e.g., sepsis; shock; severe hypovolemia; major surgery; trauma; severe metabolic, endocrine, or electrolyte disorders; or uncontrolled epilepsy).

Inform patients of the risk of myopathy and rhabdomyolysis when starting or increasing the CRESTOR dosage. Instruct patients to promptly report any unexplained muscle pain, tenderness or weakness, particularly if accompanied by malaise or fever.

5.2 Immune-Mediated Necrotizing Myopathy

There have been rare reports of immune-mediated necrotizing myopathy (IMNM), an autoimmune myopathy, associated with statin use, including reports of recurrence when the same or a different statin was administered. IMNM is characterized by proximal muscle weakness and elevated serum creatine kinase that persist despite discontinuation of statin treatment; positive anti-HMG CoA reductase antibody; muscle biopsy showing necrotizing myopathy; and improvement with immunosuppressive agents. Additional neuromuscular and serologic testing may be necessary. Treatment with immunosuppressive agents may be required. Discontinue CRESTOR if IMNM is suspected.

5.3 Hepatic Dysfunction

Increases in serum transaminases have been reported with use of CRESTOR [see Adverse Reactions (6.1)]. In most cases, these changes appeared soon after initiation, were transient, were not accompanied by symptoms, and resolved or improved on continued therapy or after a brief interruption in therapy. In a pooled analysis of placebo-controlled trials, increases in serum transaminases to more than three times the ULN occurred in 1.1% of patients taking CRESTOR versus 0.5% of patients treated with placebo. Marked persistent increases of hepatic transaminases have also occurred with CRESTOR. There have been rare postmarketing reports of fatal and non-fatal hepatic failure in patients taking statins, including CRESTOR.

Patients who consume substantial quantities of alcohol and/or have a history of liver disease may be at increased risk for hepatic injury [see Use in Specific Populations (8.7)].

Consider liver enzyme testing before CRESTOR initiation and when clinically indicated thereafter. CRESTOR is contraindicated in patients with acute liver failure or decompensated cirrhosis [see Contraindications (4)]. If serious hepatic injury with clinical symptoms and/or hyperbilirubinemia or jaundice occurs, promptly discontinue CRESTOR.

5.4 Proteinuria and Hematuria

In the CRESTOR clinical trial program, dipstick-positive proteinuria and microscopic hematuria were observed among CRESTOR treated patients. These findings were more frequent in patients taking CRESTOR 40 mg, when compared to lower doses of CRESTOR or comparator statins, though it was generally transient and was not associated with worsening renal function. Although the clinical significance of this finding is unknown, consider a dose reduction for patients on CRESTOR therapy with unexplained persistent proteinuria and/or hematuria during routine urinalysis testing.

5.5 Increases in HbA1c and Fasting Serum Glucose Levels

Increases in HbA1c and fasting serum glucose levels have been reported with statins, including CRESTOR. Based on clinical trial data with CRESTOR, in some instances these increases may exceed the threshold for the diagnosis of diabetes mellitus [see Adverse Reactions (6.1)]. Optimize lifestyle measures, including regular exercise, maintaining a healthy body weight, and making healthy food choices.

6 ADVERSE REACTIONS

The following important adverse reactions are described below and elsewhere in the labeling:

Myopathy and Rhabdomyolysis [see Warnings and Precautions (5.1)]

Immune-Mediated Necrotizing Myopathy [see Warnings and Precautions (5.2)]

Hepatic Dysfunction [see Warnings and Precautions (5.3)]

Proteinuria and Hematuria [see Warnings and Precautions (5.4)]

Increases in HbA1c and Fasting Serum Glucose Levels [see Warnings and Precautions (5.5)]

6.1 Clinical Trials Experience

Because clinical trials are conducted under widely varying conditions, adverse reaction rates observed in the clinical trials of a drug cannot be directly compared to rates in the clinical trials of another drug and may not reflect the rates observed in clinical practice.

Adverse reactions reported in ≥2% of patients in placebo-controlled clinical studies and at a rate greater than placebo are shown in Table 2. These studies had a treatment duration of up to 12 weeks.

Table 2: Adverse Reactions Reported in ≥2% of Patients Treated with CRESTOR and > Placebo in Placebo-Controlled Trials
Adverse Reactions | Placebo; N=382; % | CRESTOR; 5 mg; N=291; % | CRESTOR; 10 mg; N=283; % | CRESTOR; 20 mg; N=64; % | CRESTOR; 40 mg; N=106; % | Total; CRESTOR; 5 mg‑40 mg; N=744; %
Headache | 5.0 | 5.5 | 4.9 | 3.1 | 8.5 | 5.5
Nausea | 3.1 | 3.8 | 3.5 | 6.3 | 0 | 3.4
Myalgia | 1.3 | 3.1 | 2.1 | 6.3 | 1.9 | 2.8
Asthenia | 2.6 | 2.4 | 3.2 | 4.7 | 0.9 | 2.7
Constipation | 2.4 | 2.1 | 2.1 | 4.7 | 2.8 | 2.4

Other adverse reactions reported in clinical studies were abdominal pain, dizziness, hypersensitivity (including rash, pruritus, urticaria, and angioedema) and pancreatitis. The following laboratory abnormalities have also been reported: dipstick-positive proteinuria and microscopic hematuria; elevated creatine phosphokinase, transaminases, glucose, glutamyl transpeptidase, alkaline phosphatase, and bilirubin; and thyroid function abnormalities.

In the METEOR study, patients were treated with CRESTOR 40 mg (n=700) or placebo (n=281) with a mean treatment duration of 1.7 years. Adverse reactions reported in ≥2% of patients and at a rate greater than placebo are shown in Table 3.

Table 3: Adverse Reactions Reported in ≥2% of Patients Treated with CRESTOR and > Placebo in the METEOR Trial
Adverse Reactions | Placebo N=281 % | CRESTOR 40 mg N=700 %
Myalgia | 12.1 | 12.7
Arthralgia | 7.1 | 10.1
Headache | 5.3 | 6.4
Dizziness | 2.8 | 4.0
Increased CPK | 0.7 | 2.6
Abdominal pain | 1.8 | 2.4
ALT greater than 3x ULN [Frequency recorded as abnormal laboratory value.] | 0.7 | 2.2

In the JUPITER study, patients were treated with CRESTOR 20 mg (n=8,901) or placebo (n=8,901) for a mean duration of 2 years. In JUPITER, there was a significantly higher frequency of diabetes mellitus reported in patients taking CRESTOR (2.8%) versus patients taking placebo (2.3%). Mean HbA1c was significantly increased by 0.1% in CRESTOR-treated patients compared to placebo-treated patients. The number of patients with a HbA1c >6.5% at the end of the trial was significantly higher in CRESTOR-treated versus placebo-treated patients [see Clinical Studies (14)].

Adverse reactions reported in ≥2% of patients and at a rate greater than placebo are shown in Table 4.

Table 4: Adverse Reactions Reported in ≥2% of Patients Treated with CRESTOR and > Placebo in the JUPITER Trial
Adverse Reactions | Placebo; N=8901; % | CRESTOR 20 mg; N=8901; %
Myalgia | 6.6 | 7.6
Arthralgia | 3.2 | 3.8
Constipation | 3.0 | 3.3
Diabetes mellitus | 2.3 | 2.8
Nausea | 2.3 | 2.4

Pediatric Patients with HeFH

In a 12‑week controlled study in pediatric patients 10 to 17 years of age with HeFH with CRESTOR 5 mg to 20 mg daily [see Use in Specific Populations (8.4) and Clinical Studies (14)], elevations in serum CK greater than 10 x ULN were observed more frequently in CRESTOR-treated patients compared with patients receiving placebo. Four of 130 (3%) patients treated with CRESTOR (2 treated with 10 mg and 2 treated with 20 mg) had increased CK greater than 10 x ULN, compared to 0 of 46 patients on placebo.

6.2 Postmarketing Experience

The following adverse reactions have been identified during postapproval use of CRESTOR. Because these reactions are reported voluntarily from a population of uncertain size, it is not always possible to reliably estimate their frequency or establish a causal relationship to drug exposure.

Blood Disorders: thrombocytopenia

Hepatobiliary Disorders: hepatitis, jaundice, fatal and non-fatal hepatic failure

Musculoskeletal Disorders: arthralgia, rare reports of immune-mediated necrotizing myopathy associated with statin use

Nervous System Disorders: peripheral neuropathy, rare postmarketing reports of cognitive impairment (e.g., memory loss, forgetfulness, amnesia, memory impairment, and confusion) associated with the use of all statins. The reports are generally nonserious, and reversible upon statin discontinuation, with variable times to symptom onset (1 day to years) and symptom resolution (median of 3 weeks). There have been rare reports of new-onset or exacerbation of myasthenia gravis, including ocular myasthenia, and reports of recurrence when the same or a different statin was administered.

Psychiatric Disorders: depression, sleep disorders (including insomnia and nightmares)

Reproductive System and Breast Disorders: gynecomastia

Respiratory Disorders: interstitial lung disease

Skin and Subcutaneous Tissue Disorders: drug reaction with eosinophilia and systemic symptoms (DRESS), lichenoid drug eruption

7 DRUG INTERACTIONS

7.1 Drug Interactions that Increase the Risk of Myopathy and Rhabdomyolysis with CRESTOR

Rosuvastatin is a substrate of CYP2C9 and transporters (such as OATP1B1, BCRP). Rosuvastatin plasma levels can be significantly increased with concomitant administration of inhibitors of CYP2C9 and transporters. Table 5 includes a list of drugs that increase the risk of myopathy and rhabdomyolysis when used concomitantly with CRESTOR and instructions for preventing or managing them [see Warnings and Precautions (5.1) and Clinical Pharmacology (12.3)].

Table 5: Drug Interactions that Increase the Risk of Myopathy and Rhabdomyolysis with CRESTOR
Cyclosporine
Clinical Impact: | Cyclosporine increased rosuvastatin exposure 7-fold. The risk of myopathy and rhabdomyolysis is increased with concomitant use of cyclosporine or gemfibrozil with CRESTOR.
Intervention: | If used concomitantly, do not exceed a dose of CRESTOR 5 mg once daily.
Teriflunomide
Clinical Impact: | Teriflunomide increased rosuvastatin exposure more than 2.5-fold. The risk of myopathy and rhabdomyolysis is increased with concomitant use.
Intervention: | In patients taking teriflunomide, do not exceed a dose of CRESTOR 10 mg once daily.
Enasidenib
Clinical Impact: | Enasidenib increased rosuvastatin exposure more than 2.4-fold. The risk of myopathy and rhabdomyolysis is increased with concomitant use.
Intervention: | In patients taking enasidenib, do not exceed a dose of CRESTOR 10 mg once daily.
Capmatinib
Clinical Impact: | Capmatinib increased rosuvastatin exposure more than 2.1-fold. The risk of myopathy and rhabdomyolysis is increased with concomitant use.
Intervention: | In patients taking capmatinib, do not exceed a dose of CRESTOR 10 mg once daily.
Fostamatinib
Clinical Impact: | Fostamatinib increased rosuvastatin exposure more than 2.0-fold. The risk of myopathy and rhabdomyolysis is increased with concomitant use.
Intervention: | In patients taking fostamatinib, do not exceed a dose of CRESTOR 20 mg once daily.
Febuxostat
Clinical Impact: | Febuxostat increased rosuvastatin exposure more than 1.9-fold. The risk of myopathy and rhabdomyolysis is increased with concomitant use.
Intervention: | In patients taking febuxostat, do not exceed a dose of CRESTOR 20 mg once daily.
Gemfibrozil
Clinical Impact: | Gemfibrozil significantly increased rosuvastatin exposure and gemfibrozil may cause myopathy when given alone. The risk of myopathy and rhabdomyolysis is increased with concomitant use of gemfibrozil with CRESTOR.
Intervention: | Avoid concomitant use of gemfibrozil with CRESTOR. If used concomitantly, initiate CRESTOR at 5 mg once daily and do not exceed a dose of CRESTOR 10 mg once daily.
Tafamidis
Clinical Impact: | Tafamidis significantly increased rosuvastatin exposure and tafamidis may cause myopathy when given alone. The risk of myopathy and rhabdomyolysis is increased with concomitant use of tafamidis with CRESTOR.
Intervention: | Avoid concomitant use of tafamidis with CRESTOR. If used concomitantly, initiate CRESTOR at 5 mg once daily and do not exceed a dose of CRESTOR 20 mg once daily. Monitor for signs of myopathy and rhabdomyolysis if used concomitantly with CRESTOR.
Anti-Viral Medications
Clinical Impact: | Rosuvastatin plasma levels were significantly increased with concomitant administration of many anti-viral drugs, which increases the risk of myopathy and rhabdomyolysis.
Intervention: | - Sofosbuvir/velpatasvir/voxilaprevir - Ledipasvir/sofosbuvir | Avoid concomitant use with CRESTOR.
 | - Simeprevir - Dasabuvir/ombitasvir/paritaprevir/ritonavir - Elbasvir/grazoprevir - Sofosbuvir/velpatasvir - Glecaprevir/pibrentasvir - Atazanavir/ritonavir - Lopinavir/ritonavir | Initiate with CRESTOR 5 mg once daily, and do not exceed a dose of CRESTOR 10 mg once daily.
Darolutamide
Clinical Impact: | Darolutamide increased rosuvastatin exposure more than 5-fold. The risk of myopathy and rhabdomyolysis is increased with concomitant use.
Intervention: | In patients taking darolutamide, do not exceed a dose of CRESTOR 5 mg once daily.
Regorafenib
Clinical Impact: | Regorafenib increased rosuvastatin exposure and may increase the risk of myopathy.
Intervention: | In patients taking regorafenib, do not exceed a dose of CRESTOR 10 mg once daily.
Fenofibrates (e.g., fenofibrate and fenofibric acid)
Clinical Impact: | Fibrates may cause myopathy when given alone. The risk of myopathy and rhabdomyolysis is increased with concomitant use of fibrates with CRESTOR.
Intervention: | Consider if the benefit of using fibrates concomitantly with CRESTOR outweighs the increased risk of myopathy and rhabdomyolysis. If concomitant use is decided, monitor patients for signs and symptoms of myopathy, particularly during initiation of therapy and during upward dose titration of either drug.
Niacin
Clinical Impact: | Cases of myopathy and rhabdomyolysis have occurred with concomitant use of lipid-modifying doses (≥1 g/day) of niacin with CRESTOR.
Intervention: | Consider if the benefit of using lipid-modifying doses (≥1 g/day) of niacin concomitantly with CRESTOR outweighs the increased risk of myopathy and rhabdomyolysis. If concomitant use is decided, monitor patients for signs and symptoms of myopathy, particularly during initiation of therapy and during upward dose titration of either drug.
Colchicine
Clinical Impact: | Cases of myopathy and rhabdomyolysis have been reported with concomitant use of colchicine with CRESTOR.
Intervention: | Consider if the benefit of using colchicine concomitantly with CRESTOR outweighs the increased risk of myopathy and rhabdomyolysis. If concomitant use is decided, monitor patients for signs and symptoms of myopathy, particularly during initiation of therapy and during upward dose titration of either drug.
Ticagrelor
Clinical Impact: | Concomitant use of CRESTOR and ticagrelor has been shown to increase rosuvastatin concentrations, which may result in increased risk of myopathy. Cases of myopathy and rhabdomyolysis have been reported in patients using both products concomitantly. Cases have occurred more frequently in patients taking 40 mg of rosuvastatin.
Intervention: | In patients taking concomitant ticagrelor, especially those with additional risk factors for myopathy and rhabdomyolysis, monitor patients for signs and symptoms of myopathy, particularly during initiation of therapy and during upward dose titration of CRESTOR.

7.2 Drug Interactions that Decrease the Efficacy of CRESTOR

Table 6 presents drug interactions that may decrease the efficacy of CRESTOR and instructions for preventing or managing them.

Table 6: Drug Interactions that Decrease the Efficacy of CRESTOR
Antacids
Clinical Impact: | Concomitant aluminum and magnesium hydroxide combination antacid administration decreased the mean exposure of rosuvastatin 50% [see Clinical Pharmacology (12.3)].
Intervention: | In patients taking antacid, administer CRESTOR at least 2 hours before the antacid.

7.3 CRESTOR Effects on Other Drugs

Table 7 presents CRESTOR’s effect on other drugs and instructions for preventing or managing them.

Table 7: CRESTOR Effects on Other Drugs
Warfarin
Clinical Impact: | Rosuvastatin significantly increased the INR in patients receiving warfarin [see Clinical Pharmacology (12.3)].
Intervention: | In patients taking warfarin, obtain an INR before starting CRESTOR and frequently enough after initiation, dose titration or discontinuation to ensure that no significant alteration in INR occurs. Once the INR is stable, monitor INR at regularly recommended intervals.

8 USE IN SPECIFIC POPULATIONS

8.1 Pregnancy

Risk Summary

Discontinue CRESTOR when pregnancy is recognized. Alternatively, consider the ongoing therapeutic needs of the individual patient.

CRESTOR decreases synthesis of cholesterol and possibly other biologically active substances derived from cholesterol; therefore, CRESTOR may cause fetal harm when administered to pregnant patients based on the mechanism of action [see Clinical Pharmacology (12.1)]. In addition, treatment of hyperlipidemia is not generally necessary during pregnancy. Atherosclerosis is a chronic process and the discontinuation of lipid-lowering drugs during pregnancy should have little impact on the outcome of long-term therapy of primary hyperlipidemia for most patients.

Available data from case series and prospective and retrospective observational cohort studies over decades of use with statins in pregnant women have not identified a drug-associated risk of major congenital malformations. Published data from prospective and retrospective observational cohort studies with CRESTOR use in pregnant women are insufficient to determine if there is a drug-associated risk of miscarriage (see Data).

In animal reproduction studies, no adverse developmental effects were observed in pregnant rats or rabbits orally administered rosuvastatin during the period of organogenesis at doses that resulted in systemic exposures equivalent to human exposures at the maximum recommended human dose (MRHD) of 40 mg/day, based on AUC and body surface area (mg/m2), respectively (see Data).

The estimated background risk of major birth defects and miscarriage for the indicated population is unknown. In the U.S. general population, the estimated background risk of major birth defects and miscarriage in clinically recognized pregnancies is 2 to 4% and 15 to 20%, respectively.

Data

Human Data

A Medicaid cohort linkage study of 1,152 statin-exposed pregnant women compared to 886,996 controls did not find a significant teratogenic effect from maternal use of statins in the first trimester of pregnancy, after adjusting for potential confounders – including maternal age, diabetes mellitus, hypertension, obesity, and alcohol and tobacco use – using propensity score-based methods. The relative risk of congenital malformations between the group with statin use and the group with no statin use in the first trimester was 1.07 (95% confidence interval 0.85 to 1.37) after controlling for confounders, particularly pre-existing diabetes mellitus. There were also no statistically significant increases in any of the organ-specific malformations assessed after accounting for confounders. In the majority of pregnancies, statin treatment was initiated prior to pregnancy and was discontinued at some point in the first trimester when pregnancy was identified. Study limitations include reliance on physician coding to define the presence of a malformation, lack of control for certain confounders such as body mass index, use of prescription dispensing as verification for the use of a statin, and lack of information on non-live births.

Animal Data

In female rats given 5, 15 and 50 mg/kg/day before mating and continuing through to gestation day 7 resulted in decreased fetal body weight (female pups) and delayed ossification at 50 mg/kg/day (10 times the human exposure at the MRHD dose of 40 mg/day based on AUC).

In pregnant rats given 2, 10 and 50 mg/kg/day of rosuvastatin from gestation day 7 through lactation day 21 (weaning), decreased pup survival occurred at 50 mg/kg/day (dose equivalent to 12 times the MRHD of 40 mg/day based body surface area).

In pregnant rabbits given 0.3, 1, and 3 mg/kg/day of rosuvastatin from gestation day 6 to day 18, decreased fetal viability and maternal mortality was observed at 3 mg/kg/day (dose equivalent to the MRHD of 40 mg/day based on body surface area).

Rosuvastatin crosses the placenta in rats and rabbits and is found in fetal tissue and amniotic fluid at 3% and 20%, respectively, of the maternal plasma concentration following a single 25 mg/kg oral gavage dose on gestation day 16 in rats. In rabbits, fetal tissue distribution was 25% of maternal plasma concentration after a single oral gavage dose of 1 mg/kg on gestation day 18.

8.2 Lactation

Risk Summary

Limited data from case reports in published literature indicate that CRESTOR is present in human milk. There is no available information on the effects of the drug on the breastfed infant or the effects of the drug on milk production. Statins, including CRESTOR, decrease cholesterol synthesis and possibly the synthesis of other biologically active substances derived from cholesterol and may cause harm to the breastfed infant.

Because of the potential for serious adverse reactions in a breastfed infant, based on the mechanism of action, advise patients that breastfeeding is not recommended during treatment with CRESTOR [see Use in Specific Populations (8.1) and Clinical Pharmacology (12.1)].

8.4 Pediatric Use

The safety and effectiveness of CRESTOR as an adjunct to diet to reduce LDL-C have been established in pediatric patients 8 years of age and older with HeFH. Use of CRESTOR for this indication is based on one 12-week controlled trial with a 40-week open-label extension period in 176 pediatric patients 10 years of age and older with HeFH and one 2‑year open-label, uncontrolled trial in 175 pediatric patients 8 years of age and older with HeFH [see Clinical Studies (14)]. In the 1-year trial with a 12-week controlled phase, there was no detectable effect of CRESTOR on growth, weight, BMI (body mass index), or sexual maturation in patients aged 10 to 17 years.

The safety and effectiveness of CRESTOR as an adjunct to other LDL-C-lowering therapies to reduce LDL-C have been established in pediatric patients 7 years of age and older with HoFH. Use of CRESTOR for this indication is based on a randomized, placebo-controlled, cross-over study in 14 pediatric patients 7 years of age and older with HoFH [see Clinical Studies (14)].

The safety and effectiveness of CRESTOR have not been established in pediatric patients younger than 8 years of age with HeFH, younger than 7 years of age with HoFH, or in pediatric patients with other types of hyperlipidemia (other than HeFH or HoFH).

8.5 Geriatric Use

Of the 10,275 patients in clinical studies with CRESTOR, 3,159 (31%) were 65 years and older, and 698 (6.8%) were 75 years and older. No overall differences in safety or effectiveness were observed between these subjects and younger subjects.

Advanced age (≥65 years) is a risk factor for CRESTOR-associated myopathy and rhabdomyolysis. Dose selection for an elderly patient should be cautious, recognizing the greater frequency of decreased hepatic, renal, or cardiac function, and of concomitant disease or other drug therapy and the higher risk of myopathy. Monitor geriatric patients receiving CRESTOR for the increased risk of myopathy [see Warnings and Precautions (5.1)].

8.6 Renal Impairment

Rosuvastatin exposure is not influenced by mild to moderate renal impairment (CLcr ≥30 mL/min/1.73 m^2). Exposure to rosuvastatin is increased to a clinically significant extent in patients with severe renal impairment (CLcr <30 mL/min/1.73 m^2) who are not receiving hemodialysis [see Clinical Pharmacology (12.3)].

Renal impairment is a risk factor for myopathy and rhabdomyolysis. Monitor all patients with renal impairment for development of myopathy. In patients with severe renal impairment not on hemodialysis, the recommended starting dosage is 5 mg daily and should not exceed 10 mg daily [see Dosage and Administration (2.5) and Warnings and Precautions (5.1)].

8.7 Hepatic Impairment

CRESTOR is contraindicated in patients with acute liver failure or decompensated cirrhosis. Chronic alcohol liver disease is known to increase rosuvastatin exposure. Patients who consume substantial quantities of alcohol and/or have a history of liver disease may be at increased risk for hepatic injury [see Contraindications (4), Warning and Precautions (5.3) and Clinical Pharmacology (12.3)].

8.8 Asian Patients

Pharmacokinetic studies have demonstrated an approximate 2‑fold increase in median exposure to rosuvastatin in Asian subjects when compared with White controls. Adjust the CRESTOR dosage in Asian patients [see Dosage and Administration (2.4) and Clinical Pharmacology (12.3)].

10 OVERDOSAGE

No specific antidotes for CRESTOR are known. Hemodialysis does not significantly enhance clearance of rosuvastatin. In the event of overdose, consider contacting the Poison Help line (1-800-222-1222) or a medical toxicologist for additional overdosage management recommendations.

11 DESCRIPTION

CRESTOR (rosuvastatin) is a 3-hydroxy-3-methylglutaryl coenzyme A (HMG CoA)-reductase inhibitor.

The chemical name for rosuvastatin calcium is bis[(E)-7-[4-(4-fluorophenyl)-6-isopropyl-2-[methyl(methylsulfonyl)amino] pyrimidin-5-yl](3R,5S)-3,5-dihydroxyhept-6-enoic acid] calcium salt with the following structural formula:

The empirical formula for rosuvastatin calcium is (C22H27FN3O6S)2Ca and the molecular weight is 1,001.14. Rosuvastatin calcium is a white amorphous powder that is sparingly soluble in water and methanol, and slightly soluble in ethanol. Rosuvastatin calcium is a hydrophilic compound with a partition coefficient (octanol/water) of 0.13 at pH of 7.0.

CRESTOR tablets for oral use contain rosuvastatin 5 mg, 10 mg, 20 mg, or 40 mg (equivalent to 5.2 mg, 10.4 mg, 20.8 mg, and 41.6 mg rosuvastatin calcium) and the following inactive ingredients: crospovidone NF, hypromellose NF, lactose monohydrate NF, magnesium stearate NF, microcrystalline cellulose NF, red ferric oxide NF, titanium dioxide USP, triacetin NF, tribasic calcium phosphate NF and yellow ferric oxide.

12 CLINICAL PHARMACOLOGY

12.1 Mechanism of Action

CRESTOR is an inhibitor of HMG‑CoA reductase, the rate-limiting enzyme that converts 3‑hydroxy‑3‑methylglutaryl coenzyme A to mevalonate, a precursor of cholesterol.

12.2 Pharmacodynamics

Inhibition of HMG-CoA reductase by rosuvastatin accelerates the expression of LDL-receptors, followed by the uptake of LDL-C from blood to the liver, leading to a decrease in plasma LDL-C and total cholesterol. Sustained inhibition of cholesterol synthesis in the liver also decreases levels of very-low-density lipoproteins. The maximum LDL-C reduction of CRESTOR is usually achieved by 4 weeks and is maintained after that.

12.3 Pharmacokinetics

Absorption

In clinical pharmacology studies in man, peak plasma concentrations of rosuvastatin were reached 3 to 5 hours following oral dosing. Both Cmax and AUC increased in approximate proportion to CRESTOR dose. The absolute bioavailability of rosuvastatin is approximately 20%. The AUC of rosuvastatin does not differ following evening or morning drug administration.

Effect of food

Administration of CRESTOR with food did not affect the AUC of rosuvastatin.

Distribution

Mean volume of distribution at steady-state of rosuvastatin is approximately 134 liters. Rosuvastatin is 88% bound to plasma proteins, mostly albumin. This binding is reversible and independent of plasma concentrations.

Elimination

Metabolism

Rosuvastatin is not extensively metabolized; approximately 10% of a radiolabeled dose is recovered as metabolite. The major metabolite is N-desmethyl rosuvastatin, which is formed principally by cytochrome P450 \ 2C9, and in vitro studies have demonstrated that N-desmethyl rosuvastatin has approximately one-sixth to one-half the HMG‑CoA reductase inhibitory activity of the parent compound. Overall, greater than 90% of active plasma HMG‑CoA reductase inhibitory activity is accounted for by the parent compound.

Excretion

Following oral administration, rosuvastatin and its metabolites are primarily excreted in the feces (90%). After an intravenous dose, approximately 28% of total body clearance was via the renal route, and 72% by the hepatic route. The elimination half-life of rosuvastatin is approximately 19 hours.

Specific Populations

Geriatric Patients

There were no differences in plasma concentrations of rosuvastatin between the nonelderly and elderly populations (age ≥65 years).

Pediatric Patients

In a population pharmacokinetic analysis of two pediatric trials involving patients with HeFH 10 to 17 years of age and 8 to 17 years of age, respectively, rosuvastatin exposure appeared comparable to or lower than rosuvastatin exposure in adult patients.

Male and Female Patients

There were no differences in plasma concentrations of rosuvastatin between males and females.

Racial or Ethnic Groups

A population pharmacokinetic analysis revealed no clinically relevant differences in pharmacokinetics among White, Hispanic or Latino ethnicity, and Black or Afro-Caribbean groups. However, pharmacokinetic studies, including one conducted in the US, have demonstrated an approximate 2 fold elevation in median exposure (AUC and Cmax) in Asian subjects when compared with a White control group.

Patients with Renal Impairment

Mild to moderate renal impairment (CLcr ≥30 mL/min/1.73 m2) had no influence on plasma concentrations of rosuvastatin. However, plasma concentrations of rosuvastatin increased to a clinically significant extent (about 3‑fold) in patients with severe renal impairment (CLcr <30 mL/min/1.73 m2) not receiving hemodialysis compared with healthy subjects (CLcr >80 mL/min/1.73 m2).

Steady-state plasma concentrations of rosuvastatin in patients on chronic hemodialysis were approximately 50% greater compared with healthy volunteer subjects with normal renal function.

Patients with Hepatic Impairment

In patients with chronic alcohol liver disease, plasma concentrations of rosuvastatin were modestly increased.

In patients with Child‑Pugh A disease, Cmax and AUC were increased by 60% and 5%, respectively, as compared with patients with normal liver function. In patients with Child‑Pugh B disease, Cmax and AUC were increased 100% and 21%, respectively, compared with patients with normal liver function.

Drug Interactions Studies

Rosuvastatin clearance is not dependent on metabolism by cytochrome P450 3A4 to a clinically significant extent.

Rosuvastatin is a substrate for certain transporter proteins including the hepatic uptake transporter organic anion-transporting polyprotein 1B1 (OATP1B1) and efflux transporter breast cancer resistance protein (BCRP). Concomitant administration of CRESTOR with medications that are inhibitors of these transporter proteins (e.g., cyclosporine, certain HIV protease inhibitors [see Dosage and Administration (2.6) and Drug Interactions (7.1)] and ticagrelor [see Drug Interactions (7.1)]) may result in increased rosuvastatin plasma concentrations.

Table 8: Effect of Coadministered Drugs on Rosuvastatin Systemic Exposure
Coadministered drug and dosing regimen | Rosuvastatin
 |  | Mean Ratio (ratio with/without coadministered drug) No Effect=1.0
 | Dose (mg) [Single dose unless otherwise noted.] | Change in AUC | Change in Cmax
Sofosbuvir/velpatasvir/voxilaprevir (400 mg-100 mg-100 mg) + Voxilaprevir (100 mg) once daily for 15 days | 10 mg, single dose | 7.39 [Clinically significant [see Dosage and Administration (2) and Warnings and Precautions (5)]]; (6.68 to 8.18) [Mean ratio with 90% CI (with/without coadministered drug, e.g., 1= no change, 0.7 = 30% decrease, 11=11‑fold increase in exposure)] | 18.88; (16.23 to 21.96)
Cyclosporine – stable dose required (75 mg – 200 mg BID) | 10 mg, QD for 10 days | 7.1 | 11
Darolutamide 600 mg BID, 5 days | 5 mg, single dose | 5.2 | ~5
Regorafenib 160 mg QD, 14 days | 5 mg, single dose | 3.8 | 4.6
Atazanavir/ritonavir combination 300 mg/100 mg QD for 8 days | 10 mg | 3.1 | 7
Simeprevir 150 mg QD, 7 days | 10 mg, single dose | 2.8; (2.3 to 3.4) | 3.2; (2.6 to 3.9)
Velpatasvir 100 mg once daily | 10 mg, single dose | 2.69; (2.46 to 2.94) | 2.61; (2.32 to 2.92)
Ombitasvir 25 mg/paritaprevir 150 mg/ ritonavir 100 mg + dasabuvir 400 mg BID | 5 mg, single dose | 2.59; (2.09 to 3.21) | 7.13; (5.11 to 9.96)
Teriflunomide | Not available | 2.51 | 2.65
Enasidenib 100 mg QD, 28 days | 10 mg, single dose | 2.44 | 3.66
Elbasvir 50 mg/grazoprevir 200 mg once daily | 10 mg, single dose | 2.26; (1.89 to 2.69) | 5.49; (4.29 to 7.04)
Glecaprevir 400 mg/pibrentasvir 120 mg once daily | 5 mg, once daily | 2.15; (1.88 to 2.46) | 5.62; (4.80 to 6.59)
Lopinavir/ritonavir combination 400 mg/100 mg BID for 17 days | 20 mg, QD for 7 days | 2.1; (1.7 to 2.6) | 5; (3.4 to 6.4)
Capmatinib 400 mg BID | 10 mg, single dose | 2.08; (1.56 to 2.76) | 3.04; (2.36 to 3.92)
Fostamatinib 100 mg BID | 20 mg, single dose | 1.96; (1.77 to 2.15) | 1.88; (1.69 to 2.09)
Febuxostat 120 mg QD for 4 days | 10 mg, single dose | 1.9; (1.5 to 2.5) | 2.1; (1.8 to 2.6)
Gemfibrozil 600 mg BID for 7 days | 80 mg | 1.9; (1.6 to 2.2) | 2.2; (1.8 to 2.7)
Tafamidis 61 mg BID on Days 1 & 2, followed by QD on Days 3 to 9 | 10 mg | 1.97; (1.68 to 2.31) | 1.86; (1.59 to 2.16)
Eltrombopag 75 mg QD, 5 days | 10 mg | 1.6; (1.4 to 1.7) | 2; (1.8 to 2.3)
Darunavir 600 mg/ritonavir 100 mg BID, 7 days | 10 mg, QD for 7 days | 1.5; (1.0 to 2.1) | 2.4; (1.6 to 3.6)
Tipranavir/ritonavir combination 500 mg/200 mg BID for 11 days | 10 mg | 1.4; (1.2 to 1.6) | 2.2; (1.8 to 2.7)
Dronedarone 400 mg BID | 10 mg | 1.4
Itraconazole 200 mg QD, 5 days | 10 mg or 80 mg | 1.4; (1.2 to 1.6); 1.3; (1.1 to 1.4) | 1.4; (1.2 to 1.5); 1.2; (0.9 to 1.4)
Ezetimibe 10 mg QD, 14 days | 10 mg, QD for 14 days | 1.2 (0.9 to 1.6) | 1.2; (0.8 to 1.6)
Fosamprenavir/ritonavir 700 mg/100 mg BID for 7 days | 10 mg | 1.1 | 1.5
Fenofibrate 67 mg TID for 7 days | 10 mg | ↔ | 1.2; (1.1 to 1.3)
Rifampicin 450 mg QD, 7 days | 20 mg | ↔
Aluminum & magnesium hydroxide combination antacid; Administered simultaneously Administered 2 hours apart | 40 mg 40 mg | 0.5; (0.4 to 0.5) 0.8; (0.7 to 0.9) | 0.5; (0.4 to 0.6) 0.8; (0.7 to 1.0)
Ketoconazole 200 mg BID for 7 days | 80 mg | 1.0; (0.8 to 1.2) | 1.0; (0.7 to 1.3)
Fluconazole 200 mg QD for 11 days | 80 mg | 1.1; (1.0 to 1.3) | 1.1; (0.9 to 1.4)
Erythromycin 500 mg QID for 7 days | 80 mg | 0.8; (0.7 to 0.9) | 0.7; (0.5 to 0.9)
QD= Once daily, BID= Twice daily, TID= Three times daily, QID= Four times daily

Table 9: Effect of Rosuvastatin Coadministration on Systemic Exposure to Other Drugs
Rosuvastatin Dosage Regimen | Coadministered Drug
 |  | Mean Ratio (ratio with/without coadministered drug) No Effect=1.0
 | Name and Dose | Change in AUC | Change in Cmax
40 mg QD for 10 days | Warfarin [Clinically significant pharmacodynamic effects [see Drug Interactions (7.3)]]; 25 mg single dose | R-Warfarin; 1.0; (1.0 to 1.1) [Mean ratio with 90% CI (with/without coadministered drug, e.g., 1= no change, 0.7=30% decrease, 11=11‑fold increase in exposure)]; S-Warfarin; 1.1; (1.0 to 1.1) | R-Warfarin; 1.0; (0.9 to 1.0); S-Warfarin; 1.0; (0.9 to 1.1)
40 mg QD for 12 days | Digoxin; 0.5 mg single dose | 1.0; (0.9 to 1.2) | 1.0; (0.9 to 1.2)
40 mg QD for 28 days | Oral Contraceptive; (ethinyl estradiol 0.035 mg & norgestrel 0.180, 0.215 and 0.250 mg) QD for 21 Days | EE 1.3; (1.2 to 1.3); NG 1.3; (1.3 to 1.4) | EE 1.3; (1.2 to 1.3); NG 1.2; (1.1 to 1.3)
EE = ethinyl estradiol, NG = norgestrel, QD= Once daily

12.5 Pharmacogenomics

Disposition of rosuvastatin, involves OATP1B1 and other transporter proteins. Higher plasma concentrations of rosuvastatin have been reported in very small groups of patients (n=3 to 5) who have two reduced function alleles of the gene that encodes OATP1B1 (SLCO1B1 521T > C). The frequency of this genotype (i.e., SLCO1B1 521 C/C) is generally lower than 5% in most racial/ethnic groups. The impact of this polymorphism on efficacy and/or safety of CRESTOR has not been clearly established.

13 NONCLINICAL TOXICOLOGY

13.1 Carcinogenesis, Mutagenesis, Impairment of Fertility

In a 104‑week carcinogenicity study in rats at dose levels of 2, 20, 60, or 80 mg/kg/day by oral gavage, the incidence of uterine stromal polyps was significantly increased in females at 80 mg/kg/day at systemic exposure 20 times the human exposure at 40 mg/day based on AUC. Increased incidence of polyps was not seen at lower doses.

In a 107‑week carcinogenicity study in mice given 10, 60, or 200 mg/kg/day by oral gavage, an increased incidence of hepatocellular adenoma/carcinoma was observed at 200 mg/kg/day at systemic exposures 20 times the human exposure at 40 mg/day based on AUC. An increased incidence of hepatocellular tumors was not seen at lower doses.

Rosuvastatin was not mutagenic or clastogenic with or without metabolic activation in the Ames test with Salmonella typhimurium and Escherichia coli, the mouse lymphoma assay, and the chromosomal aberration assay in Chinese hamster lung cells. Rosuvastatin was negative in the in vivo mouse micronucleus test.

In rat fertility studies with oral gavage doses of 5, 15, 50 mg/kg/day, males were treated for 9 weeks prior to and throughout mating and females were treated 2 weeks prior to mating and throughout mating until gestation day 7. No adverse effect on fertility was observed at 50 mg/kg/day (systemic exposures up to 10 times the human exposure at 40 mg/day based on AUC). In testicles of dogs treated with rosuvastatin at 30 mg/kg/day for one month, spermatidic giant cells were seen. Spermatidic giant cells were observed in monkeys after 6‑month treatment at 30 mg/kg/day in addition to vacuolation of seminiferous tubular epithelium. Exposures in the dog were 20 times and in the monkey 10 times the human exposure at 40 mg/day based on body surface area. Similar findings have been seen with other drugs in this class.

14 CLINICAL STUDIES

Primary Prevention of CV Disease

In the Justification for the Use of Statins in Primary Prevention: An Intervention Trial Evaluating Rosuvastatin (JUPITER) study, the effect of CRESTOR on the occurrence of major CV disease events was assessed in 17,802 males (≥50 years) and females (≥60 years) who had no clinically evident CV disease, LDL‑C levels <130 mg/dL and hsCRP levels ≥2 mg/L. The study population had an estimated baseline coronary heart disease risk of 11.6% over 10 years based on the Framingham risk criteria and included a high percentage of patients with additional risk factors such as hypertension (58%), low HDL‑C levels (23%), cigarette smoking (16%), or a family history of premature CHD (12%). Patients had a median baseline LDL‑C of 108 mg/dL and hsCRP of 4.3 mg/L. Patients were randomly assigned to placebo (n=8901) or CRESTOR 20 mg once daily (n=8901) and were followed for a mean duration of 2 years. The JUPITER study was stopped early by the Data Safety Monitoring Board due to meeting predefined stopping rules for efficacy in CRESTOR-treated subjects.

The primary end point was a composite end point consisting of the time-to-first occurrence of any of the following major CV events: CV death, nonfatal myocardial infarction, nonfatal stroke, hospitalization for unstable angina or an arterial revascularization procedure.

CRESTOR significantly reduced the risk of major CV events (252 events in the placebo group vs. 142 events in the rosuvastatin group) with a statistically significant (p<0.001) relative risk reduction of 44% and absolute risk reduction of 1.2% (see Figure 1). The risk reduction for the primary end point was consistent across the following predefined subgroups: age, sex, race, smoking status, family history of premature CHD, body mass index, LDL‑C, HDL‑C, and hsCRP levels.

Figure 1. Time to First Occurrence of Major CV Events in JUPITER

The individual components of the primary end point are presented in Figure 3. CRESTOR significantly reduced the risk of nonfatal myocardial infarction, nonfatal stroke, and arterial revascularization procedures. There were no significant treatment differences between the CRESTOR and placebo groups for death due to CV causes or hospitalizations for unstable angina.

CRESTOR significantly reduced the risk of myocardial infarction (6 fatal events and 62 nonfatal events in placebo-treated subjects vs. 9 fatal events and 22 nonfatal events in CRESTOR-treated subjects) and the risk of stroke (6 fatal events and 58 nonfatal events in placebo-treated subjects vs. 3 fatal events and 30 nonfatal events in CRESTOR-treated subjects).

In a post-hoc subgroup analysis of JUPITER subjects (rosuvastatin=725, placebo=680) with a hsCRP ≥2 mg/L and no other traditional risk factors (smoking, BP ≥140/90 or taking antihypertensives, low HDL‑C) other than age, after adjustment for high HDL‑C, there was no significant treatment benefit with CRESTOR treatment.

Figure 2. Major CV Events by Treatment Group in JUPITER

At one year, CRESTOR increased HDL‑C and reduced LDL‑C, hsCRP, total cholesterol and serum triglyceride levels (p<0.001 for all versus placebo).

Primary Hyperlipidemia in Adults

CRESTOR reduces Total‑C, LDL‑C, ApoB, non‑HDL‑C, and TG, and increases HDL‑C, in adult patients with hyperlipidemia and mixed dyslipidemia.

In a multicenter, double‑blind, placebo‑controlled study in patients with hyperlipidemia, CRESTOR given as a single daily dose (5 to 40 mg) for 6 weeks significantly reduced Total‑C, LDL‑C, non‑HDL‑C, and ApoB, across the dose range (Table 10).

Table 10: Lipid-Modifying Effect of CRESTOR in Adult Patients with Hyperlipidemia (Adjusted Mean % Change from Baseline at Week 6)
Dose | N | Total‑C | LDL‑C | Non-HDL‑C | ApoB | TG | HDL‑C
Placebo | 13 | -5 | -7 | -7 | -3 | -3 | 3
CRESTOR 5 mg | 17 | -33 | -45 | -44 | -38 | -35 | 13
CRESTOR 10 mg | 17 | -36 | -52 | -48 | -42 | -10 | 14
CRESTOR 20 mg | 17 | -40 | -55 | -51 | -46 | -23 | 8
CRESTOR 40 mg | 18 | -46 | -63 | -60 | -54 | -28 | 10

CRESTOR was compared with the statins (atorvastatin, simvastatin, and pravastatin) in a multicenter, open-label, dose‑ranging study of 2,240 patients with hyperlipidemia or mixed dyslipidemia. After randomization, patients were treated for 6 weeks with a single daily dose of either CRESTOR, atorvastatin, simvastatin, or pravastatin (see Figure 3 and Table 11).

Figure 3. Percent LDL‑C Change by Dose of CRESTOR, Atorvastatin, Simvastatin, and Pravastatin at Week 6 in Adult Patients with Hyperlipidemia or Mixed Dyslipidemia

Box plots are a representation of the 25th, 50th, and 75th percentile values, with whiskers representing the 10th and 90th percentile values. Mean baseline LDL‑C: 189 mg/dL.

Table 11: Percent Change in LDL-C by Dose of CRESTOR, Atorvastatin, Simvastatin, and Pravastatin From Baseline to Week 6 (LS Mean [Corresponding standard errors are approximately 1.00.]) in Adult Patients with Hyperlipidemia or Mixed Dyslipidemia (Sample Sizes Ranging from 156–167 Patients Per Group)
 | Treatment Daily Dose
Treatment | 10 mg | 20 mg | 40 mg | 80 mg
CRESTOR | -46 [CRESTOR 10 mg reduced LDL-C significantly more than atorvastatin 10 mg; pravastatin 10 mg, 20 mg, and 40 mg; simvastatin 10 mg, 20 mg, and 40 mg. (p<0.002)] | -52 [CRESTOR 20 mg reduced LDL-C significantly more than atorvastatin 20 mg and 40 mg; pravastatin 20 mg and 40 mg; simvastatin 20 mg, 40 mg, and 80 mg. (p<0.002)] | -55 [CRESTOR 40 mg reduced LDL‑C significantly more than atorvastatin 40 mg; pravastatin 40 mg; simvastatin 40 mg, and 80 mg. (p<0.002)] | ---
Atorvastatin | -37 | -43 | -48 | -51
Simvastatin | -28 | -35 | -39 | -46
Pravastatin | -20 | -24 | -30 | ---

Slowing of the Progression of Atherosclerosis

In the Measuring Effects on Intima Media Thickness: an Evaluation Of Rosuvastatin 40 mg (METEOR) study, the effect of therapy with CRESTOR on carotid atherosclerosis was assessed by B-mode ultrasonography in patients with elevated LDL‑C, at low risk (Framingham risk <10% over ten years) for symptomatic coronary artery disease and with subclinical atherosclerosis as evidenced by carotid intimal-medial thickness (cIMT). In this double-blind, placebo-controlled clinical study 984 adult patients were randomized (of whom 876 were analyzed) in a 5:2 ratio to CRESTOR 40 mg or placebo once daily. Ultrasonograms of the carotid walls were used to determine the annualized rate of change per patient from baseline to two years in mean maximum cIMT of 12 measured segments. The estimated difference in the rate of change in the maximum cIMT analyzed over all 12 carotid artery sites between patients treated with CRESTOR and placebo-treated patients was -0.0145 mm/year (95% CI –0.0196, –0.0093; p<0.0001).

The annualized rate of change from baseline for the placebo group was +0.0131 mm/year (p<0.0001). The annualized rate of change from baseline for the group treated with CRESTOR was -0.0014 mm/year (p=0.32).

At an individual patient level in the group treated with CRESTOR, 52.1% of patients demonstrated an absence of disease progression (defined as a negative annualized rate of change), compared to 37.7% of patients in the placebo group.

HeFH in Adults

In a study of adult patients with HeFH (baseline mean LDL of 291 mg/dL), patients were randomized to CRESTOR 20 mg or atorvastatin 20 mg. The dose was increased at 6-week intervals. Significant LDL-C reductions from baseline were seen at each dose in both treatment groups (see Table 12).

Table 12: LDL-C Percent Change from Baseline
 |  | CRESTOR (n=435) LS Mean [LS Means are least square means adjusted for baseline LDL-C] (95% CI) | Atorvastatin (n=187) LS Mean^1 (95% CI)
Week 6 | 20 mg | -47% (-49%, -46%) | -38% (-40%, -36%)
Week 12 | 40 mg | -55% (-57%, -54%) | -47% (-49%, -45%)
Week 18 | 80 mg | NA | -52% (-54%, -50%)

HeFH in Pediatric Patients

In a double-blind, randomized, multicenter, placebo-controlled, 12-week study, 176 (97 male and 79 female) pediatric patients with HeFH were randomized to rosuvastatin 5 mg, 10 mg or 20 mg or placebo daily. Patients ranged in age from 10 to 17 years (median age of 14 years) with approximately 30% of the patients 10 to 13 years and approximately 17%, 18%, 40%, and 25% at Tanner stages II, III, IV, and V, respectively. Females were at least 1-year postmenarche. Mean LDL-C at baseline was 233 mg/dL (range of 129 to 399). The 12-week double-blind phase was followed by a 40-week open-label dose-titration phase, where all patients (n=173) received 5 mg, 10 mg or 20 mg rosuvastatin daily.

Rosuvastatin significantly reduced LDL-C (primary end point), total cholesterol and ApoB levels at each dose compared to placebo. Results are shown in Table 13 below.

Table 13: Lipid-Modifying Effects of CRESTOR in Pediatric Patients 10 to 17 years of Age with HeFH (Least-Squares Mean Percent Change from Baseline To Week 12)
Dose (mg) | N | LDL‑C | HDL‑C | Total‑C | TG [Median percent change] | ApoB
Placebo | 46 | -1% | +7% | 0% | -7% | -2%
5 | 42 | -38% | +4% [Difference from placebo not statistically significant] | -30% | -13% | -32%
10 | 44 | -45% | +11% | -34% | -15% | -38%
20 | 44 | -50% | +9% | -39% | 16% | -41%

Rosuvastatin was also studied in a two-year open‑label, uncontrolled, titration-to-goal trial that included 175 pediatric patients with HeFH who were 8 to 17 years old (79 males and 96 females). All patients had a documented genetic defect in the LDL receptor or in ApoB. Approximately 89% were White, 7% were Asian, 1% were Black or African American, and fewer than 1% were Hispanic or Latino ethnicity. Mean LDL-C at baseline was 236 mg/dL. Fifty-eight (33%) patients were prepubertal at baseline. The starting rosuvastatin dosage for all pediatric patients was 5 mg once daily. Pediatric patients aged 8 to less than 10 years (n=41 at baseline) could titrate to a maximum dosage of 10 mg once daily, and pediatric patients aged 10 to 17 years could titrate to a maximum dosage of 20 mg once daily.

The reductions in LDL‑C from baseline were generally consistent across age groups within the trial as well as with previous experience in both adult and pediatric controlled trials.

HoFH in Adult and Pediatric Patients

In an open-label, forced-titration study, HoFH patients (n=40, 8‑63 years) were evaluated for their response to CRESTOR 20 to 40 mg titrated at a 6‑week interval. In the overall population, the mean LDL‑C reduction from baseline was 22%. About one-third of the patients benefited from increasing their dose from 20 mg to 40 mg with further LDL‑C lowering of greater than 6%. In the 27 patients with at least a 15% reduction in LDL‑C, the mean LDL‑C reduction was 30% (median 28% reduction). Among 13 patients with an LDL‑C reduction of <15%, 3 had no change or an increase in LDL‑C. Reductions in LDL‑C of 15% or greater were observed in 3 of 5 patients with known receptor negative status.

HoFH in Pediatric Patients

CRESTOR was studied in a randomized, double-blind, placebo-controlled, multicenter, cross-over study in 14 pediatric patients with HoFH. The study included a 4‑week dietary lead‑in phase during which patients received CRESTOR 10 mg daily, a cross‑over phase that included two 6‑week treatment periods with either CRESTOR 20 mg or placebo in random order, followed by a 12‑week open‑label phase during which all patients received CRESTOR 20 mg. Patients ranged in age from 7 to 15 years of age (median 11 years), 50% were male, 71% were White, 21% were Asian, 7% were Black or African American, and no patients were of Hispanic or Latino ethnicity. Fifty percent were on apheresis therapy and 57% were taking ezetimibe. Patients who entered the study on apheresis therapy or ezetimibe continued the treatment throughout the entire study. Mean LDL-C at baseline was 416 mg/dL (range 152 to 716 mg/dL). A total of 13 patients completed both treatment periods of the randomized cross-over phase; one patient withdrew consent due to inability to have blood drawn during the cross-over phase.

CRESTOR 20 mg significantly reduced LDL-C, total cholesterol, ApoB, and non-HDL-C compared to placebo (see Table 14).

Table 14: Lipid-Modifying Effects of CRESTOR in Pediatric Patients 7 to 15 years of Age with HoFH After 6 Weeks
 | Placebo; (N=13) | CRESTOR 20 mg; (N=13) | Percent difference (95% CI)
LDL-C (mg/dL) | 481 | 396 | -22.3% (-33.5, -9.1) [p=0.005]
Total-C (mg/dL) | 539 | 448 | -20.1% (-29.7, -9.1) [p=0.003]
Non-HDL-C (mg/dL) | 505 | 412 | -22.9% (-33.7, ‑10.3)
ApoB (mg/dL) | 268 | 235 | -17.1% (-29.2, -2.9) [p=0.024]
% Difference estimates are based on transformations of the estimated mean difference in log LDL measurements between CRESTOR and placebo using a mixed model adjusted for study period.

Primary Dysbetalipoproteinemia in Adults

In a randomized, multicenter, double-blind crossover-study, 32 adult patients (27 with є2/є2 and 4 with apo E mutation [Arg145Cys] with primary dysbetalipoproteinemia entered a 6‑week dietary lead-in period on the NCEP Therapeutic Lifestyle Change (TLC) diet. Following dietary lead-in, patients were randomized to a sequence of treatments for 6 weeks each: rosuvastatin 10 mg followed by rosuvastatin 20 mg or rosuvastatin 20 mg followed by rosuvastatin 10 mg. CRESTOR reduced non-HDL‑C (primary end point) and circulating remnant lipoprotein levels. Results are shown in the table below.

Table 15: Lipid-Modifying Effects of CRESTOR 10 mg and 20 mg in Adult Patients with Primary Dysbetalipoproteinemia (Type III hyperlipoproteinemia) After Six Weeks by Median Percent Change (95% CI) from Baseline (N=32)
 | Median at Baseline (mg/dL) | Median percent change from baseline (95% CI) CRESTOR 10 mg | Median percent change from baseline (95% CI) CRESTOR 20 mg
Total‑C | 342.5 | -43.3; (-46.9, - 37.5) | -47.6; (-51.6,-42.8)
Triglycerides | 503.5 | -40.1; (-44.9, -33.6) | -43.0; (-52.5, -33.1)
Non-HDL‑C | 294.5 | -48.2; (-56.7, -45.6) | -56.4; (-61.4, -48.5)
VLDL‑C + IDL‑C | 209.5 | -46.8; (-53.7, -39.4) | -56.2; (-67.7, -43.7)
LDL‑C | 112.5 | -54.4; (-59.1, -47.3) | -57.3; (-59.4, -52.1)
HDL‑C | 35.5 | 10.2; (1.9, 12.3) | 11.2; (8.3, 20.5)
RLP‑C | 82.0 | -56.4; (-67.1, -49.0) | -64.9; (-74.0, -56.6)
Apo‑E | 16.0 | -42.9; (-46.3, -33.3) | -42.5; (-47.1, -35.6)

Hypertriglyceridemia in Adults

In a double-blind, placebo-controlled study in adult patients with baseline TG levels from 273 to 817 mg/dL, CRESTOR given as a single daily dose (5 to 40 mg) over 6 weeks significantly reduced serum TG levels (Table 16).

Table 16: Lipid-Modifying Effect of CRESTOR in Adult Patients with Primary Hypertriglyceridemia After Six Weeks by Median (Min, Max) Percent Change from Baseline to Week 6
Dose | Placebo (n=26) | CRESTOR 5 mg (n=25) | CRESTOR 10 mg (n=23) | CRESTOR 20 mg (n=27) | CRESTOR 40 mg (n=25)
Triglycerides | 1 (-40, 72) | -21 (-58, 38) | -37 (-65, 5) | -37 (-72, 11) | -43 (-80, -7)
Non-HDL-C | 2 (-13, 19) | -29 (-43, -8) | -49 (-59, -20) | -43 (-74, 12) | -51 (-62, -6)
Total-C | 1 (-13, 17) | -24 (-40, -4) | -40 (-51, -14) | -34 (-61, -11) | -40 (-51, -4)
LDL-C | 5 (-30, 52) | -28 (-71, 2) | -45 (-59, 7) | -31 (-66, 34) | -43 (-61, -3)
HDL-C | -3 (-25, 18) | 3 (-38, 33) | 8 (-8, 24) | 22 (-5, 50) | 17 (-14, 63)

16 HOW SUPPLIED/STORAGE AND HANDLING

CRESTOR tablets are supplied as:

Strength | How Supplied | NDC | Tablet Description
5 mg | bottles of 90 tablets | 0310-7560-90 | Yellow, round, biconvex, coated tablets. Debossed “ZD4522” and “5” on one side
10 mg | bottles of 90 tablets | 0310-7570-90 | Pink, round, biconvex, coated tablets. Debossed “ZD4522” and “10” on one side
20 mg | bottles of 90 tablets | 0310-7580-90 | Pink, round, biconvex, coated tablets. Debossed “ZD4522” and “20” on one side
40 mg | bottles of 30 tablets | 0310-7590-30 | Pink, oval, biconvex, coated tablets. Debossed “ZD4522” on one side and “40” on the other side

Storage

Store at controlled room temperature, 20ºC to 25ºC (68ºF to 77ºF); excursions permitted between 15°C and 30°C (59°F and 86°F) [see USP Controlled Room Temperature]. Protect from moisture.

17 PATIENT COUNSELING INFORMATION

Advise the patient to read the FDA-approved patient labeling (Patient Information).

Myopathy and Rhabdomyolysis

Advise patients that CRESTOR may cause myopathy and rhabdomyolysis. Inform patients that the risk is also increased when taking certain types of medication and they should discuss all medication, both prescription and over-the-counter, with their healthcare provider. Instruct patients to promptly report any unexplained muscle pain, tenderness or weakness particularly if accompanied by malaise or fever [see Warnings and Precautions (5.1), and Drug Interactions (7.1)].

Hepatic Dysfunction

Inform patients that CRESTOR may cause liver enzyme elevations and possibly liver failure. Advise patients to promptly report fatigue, anorexia, right upper abdominal discomfort, dark urine or jaundice [see Warnings and Precautions (5.3)].

Increases in HbA1c and Fasting Serum Glucose Levels

Inform patients that increases in HbA1c and fasting serum glucose levels may occur with CRESTOR. Encourage patients to optimize lifestyle measures, including regular exercise, maintaining a healthy body weight, and making healthy food choices [see Warnings and Precautions (5.5)].

Pregnancy

Advise pregnant patients and patients who can become pregnant of the potential risk to a fetus. Advise patients to inform their healthcare provider of a known or suspected pregnancy to discuss if CRESTOR should be discontinued [see Use in Specific Populations (8.1)].

Lactation

Advise patients that breastfeeding during treatment with CRESTOR is not recommended [see Use in Specific Populations (8.2)].

Concomitant Use of Antacids

When taking CRESTOR with an aluminum and magnesium hydroxide combination antacid, administer CRESTOR at least 2 hours before the antacid [see Drug Interactions (7.2)].

Missed Doses

If a dose is missed, advise patients not take an extra dose. Just resume the usual schedule [see Dosage and Administration (2.1)].

CRESTOR® is a trademark of the AstraZeneca group of companies.

© AstraZeneca XXXX

Licensed from SHIONOGI & CO., LTD., Osaka, Japan

Distributed by:

AstraZeneca Pharmaceuticals LP

Wilmington, DE 19850

PATIENT INFORMATION

CRESTOR® (Kres-tor)

rosuvastatin

tablets, for oral use

Read this Patient Information carefully before you start taking CRESTOR and each time you get a refill. If you have any questions about CRESTOR, ask your healthcare provider. Only your healthcare provider can determine if CRESTOR is right for you.

What is CRESTOR?

CRESTOR is a prescription medicine that contains a cholesterol-lowering medicine called rosuvastatin.

- CRESTOR is used to:
  ∘ to reduce the risk of major adverse cardiovascular (CV) events, such as death from cardiovascular disease, heart attack, stroke, or the need for procedures to improve blood flow to the heart called arterial revascularization, in adults who do not have known heart disease but do have certain additional risk factors.
  ∘ along with diet to:
    - lower the level of low-density lipoprotein (LDL-C) cholesterol or “bad” cholesterol in adults with primary hyperlipidemia.
    - slow the buildup of fatty deposits (plaque) in the walls of blood vessels.
    - treat adults and children 8 years of age and older with high blood cholesterol due to heterozygous familial hypercholesterolemia (HeFH) (an inherited condition that causes high levels of LDL-C).
  ∘ along with other cholesterol lowering treatments or alone if such treatments are unavailable in adults and children 7 years of age and older with homozygous familial hypercholesterolemia (HoFH) (an inherited condition that causes high levels of LDL-C).
  ∘ along with diet for the treatment of adults with:
    - primary dysbetalipoproteinemia (an inherited condition that causes high levels of cholesterol and fat).
    - hypertriglyceridemia.

It is not known if CRESTOR is safe and effective in children younger than 8 years of age with HeFH or children younger than 7 years of age with HoFH or in children with other types of hyperlipidemias (other than HeFH or HoFH).

Do not take CRESTOR if you:

- have liver problems.
- are allergic to rosuvastatin or any of the ingredients in CRESTOR. See the end of this leaflet for a complete list of ingredients in CRESTOR. Symptoms of allergic reactions include rash, itching, hives, and swelling.

Before you take CRESTOR, tell your healthcare provider about all of your medical conditions, including if you:

- have unexplained muscle aches or weakness.
- have or have had kidney problems.
- have or have had liver problems.
- drink more than 2 glasses of alcohol daily.
- have thyroid problems.
- are of Asian descent.
- are pregnant or think you may be pregnant, or are planning to become pregnant. If you become pregnant while taking CRESTOR, call your healthcare provider right away to discuss your CRESTOR treatment.
- are breastfeeding. CRESTOR can pass into your breast milk and may harm your baby. Talk to your healthcare provider about the best way to feed your baby if you take CRESTOR. Do not breastfeed while taking CRESTOR.

Tell your healthcare provider about all the medicines you take, including prescription and over-the-counter medicines, vitamins, and herbal supplements. Tell your healthcare provider who prescribes CRESTOR if another healthcare provider increases the dose of another medicine you are taking. CRESTOR may affect the way other medicines work, and other medicines may affect how CRESTOR works.

Especially tell your healthcare provider if you take:

- coumarin anticoagulants (medicines that prevent blood clots, such as warfarin)
- antacids (medicines you take for heartburn that contain aluminum and magnesium hydroxide

Taking CRESTOR with certain medicines may increase the risk of muscle problems.

Especially tell your healthcare provider if you take:

- cyclosporine (a medicine for your immune system)
- teriflunomide (a medicine used to treat relapsing remitting multiple sclerosis)
- enasidenib (a medicine used to treat acute myeloid leukemia)
- capmatinib (a medicine for the treatment of non-small cell lung cancer)
- fostamatinib (a medicine used to treat low platelet counts)
- febuxostat (a medicine used to treat and prevent high blood levels of uric acid)
- gemfibrozil (a fibric acid medicine for lowering cholesterol)
- tafamidis [used to treat cardiomyopathy (enlarged and thickened heart muscle)]
- anti-viral medicines including certain HIV or hepatitis C virus drugs such as:
  ∘ lopinavir, ritonavir, fosamprenavir, tipranavir, atazanavir, simeprevir
  ∘ combination of
    - sofosbuvir/velpatasvir/voxilaprevir
    - dasabuvir/ombitasvir/paritaprevir/ritonavir
    - elbasvir/grazoprevir
    - sofosbuvir/velpatasvir
    - glecaprevir/pibrentasvir and
  ∘ all other combinations with ledipasvir including ledipasvir/sofosbuvir
- darolutamide (a medicine for the treatment of prostate cancer)
- regorafenib (a medicine used to treat cancer of the colon and rectum)
- fibric acid derivatives (such as fenofibrate)
- ticagrelor (helps reduce the chance of a blood clot formation that can block a blood vessel)
- niacin or nicotinic acid
- colchicine (a medicine used to treat gout)

Ask your healthcare provider or pharmacist for a list of these medicines if you are not sure. Know the medicines you take. Keep a list of them to show your healthcare provider and pharmacist when you get new medicine.

How should I take CRESTOR?

- Take CRESTOR exactly as your healthcare provider tells you to take it.
- Take CRESTOR, by mouth, 1 time each day, with or without food. Swallow the tablet whole.
- CRESTOR can be taken at any time of day, with or without food.
- Do not change your dose or stop CRESTOR without talking to your healthcare provider, even if you are feeling well.
- Your healthcare provider may do blood tests to check your cholesterol levels before and during your treatment with CRESTOR. Your healthcare provider may change your dose of CRESTOR if needed.
- While taking CRESTOR, continue to follow your cholesterol-lowering diet and to exercise as your healthcare provider told you to.
- If you take a medicine called an antacid that contains a combination of aluminum and magnesium hydroxide, take CRESTOR at least 2 hours before you take the antacid.
- If you miss a dose of CRESTOR, take your next dose at your normal scheduled time. Do not take an extra dose of CRESTOR.
- In case of an overdose, get medical help or contact a live Poison Center expert right away at 1-800-222-1222. Advice is also available online at poisonhelp.org.

What are the possible side effects of CRESTOR?

CRESTOR may cause serious side effects, including:

- Muscle pain, tenderness and weakness (myopathy). Muscle problems, including muscle breakdown, can be serious in some people and rarely cause kidney damage that can lead to death. Tell your healthcare provider right away if:
  - you have unexplained muscle pain, tenderness, or weakness, especially if you have a fever or feel more tired than usual, while you take CRESTOR.
  - you have muscle problems that do not go away even after your healthcare provider has told you to stop taking CRESTOR. Your healthcare provider may do further tests to diagnose the cause of your muscle problems.

Your chances of getting muscle problems are higher if you:

  - are taking certain other medicines while you take CRESTOR (see “Especially tell your healthcare provider if you take”)
  - are 65 years of age or older
  - are of Asian descent
  - have thyroid problems (hypothyroidism) that are not controlled
  - have kidney problems
  - are taking higher doses of CRESTOR
- Liver problems. Your healthcare provider may do blood tests to check your liver before you start taking CRESTOR and if you have symptoms of liver problems while you take CRESTOR. Call your healthcare provider right away if you have any of the following symptoms of liver problems:
  - feel unusually tired or weak
  - loss of appetite
  - upper belly pain
  - dark urine
  - yellowing of your skin or the whites of your eyes
- Protein and blood in the urine. CRESTOR may cause you to have protein and blood in your urine. If you develop protein or blood in your urine, your healthcare provider may decrease your dose of CRESTOR.
- Increase in blood sugar (glucose) levels. CRESTOR may cause an increase in your blood sugar levels.

The most common side effects may include headache, nausea, muscle aches and pains, weakness, and constipation.

Tell your healthcare provider if you have any side effect that bothers you or that does not go away.

For more information, ask your healthcare provider or pharmacist.

Call your doctor for medical advice about side effects. You may report side effects to FDA at 1-800-FDA-1088.

How should I store CRESTOR?

- Store CRESTOR at room temperature, between 68°F to 77°F (20°C to 25°C) and in a dry place.

Keep CRESTOR and all medicines out of the reach of children.

General Information about the safe and effective use of CRESTOR

Medicines are sometimes prescribed for purposes other than those listed in a Patient Information leaflet. Do not use CRESTOR for a condition for which it was not prescribed. Do not give CRESTOR to other people, even if they have the same medical condition you have. It may harm them.

You can ask your pharmacist or healthcare provider for information about CRESTOR that is written for health professionals.

What are the Ingredients in CRESTOR?

Active Ingredient: rosuvastatin as rosuvastatin calcium

Inactive Ingredients: crospovidone NF, hypromellose NF, lactose monohydrate NF, magnesium stearate NF, microcrystalline cellulose NF, red ferric oxide NF, titanium dioxide USP, triacetin NF, tribasic calcium phosphate NF and yellow ferric oxide.

CRESTOR® is a trademark of the AstraZeneca group of companies.

© AstraZeneca 2024

Licensed from SHIONOGI & CO., LTD., Osaka, Japan

Distributed by:

AstraZeneca Pharmaceuticals LP

Wilmington, DE 19850

For more information, go to the CRESTOR website at www.crestor.com or call 1-800-CRESTOR

This Patient Information has been approved by the U.S. Food and Drug Administration Revised 07/2024

Package/Label Display Panel – 5 mg

NDC 0310-7560-90 90 tablets

CRESTOR®

rosuvastatin

5 mg tablets

Rx only

Mfd. for: AstraZeneca Pharmaceuticals LP

Wilmington, DE 19850

By: IPR Pharmaceuticals, Inc.

Canóvanas, PR 00729

Product of Switzerland

AstraZeneca

Package/Label Display Panel – 10 mg

NDC 0310-7570-90 90 tablets

CRESTOR®

rosuvastatin

10 mg tablets

Rx only

Mfd. for: AstraZeneca Pharmaceuticals LP

Wilmington, DE 19850

By: IPR Pharmaceuticals, Inc.

Canóvanas, PR 00729

Product of Switzerland

AstraZeneca

Package/Label Display Panel – 20 mg

NDC 0310-7580-90 90 tablets

CRESTOR®

rosuvastatin

20 mg tablets

Rx only

Mfd. for: AstraZeneca Pharmaceuticals LP

Wilmington, DE 19850

By: IPR Pharmaceuticals, Inc.

Canóvanas, PR 00729

Product of Switzerland

AstraZeneca

Package/Label Display Panel – 40 mg

NDC 0310-7590-30 30 tablets

CRESTOR®

rosuvastatin

40 mg tablets

Rx only

Mfd. for: AstraZeneca Pharmaceuticals LP

Wilmington, DE 19850

By: IPR Pharmaceuticals Inc

Canóvanas, PR 00729

Product of Switzerland

AstraZeneca